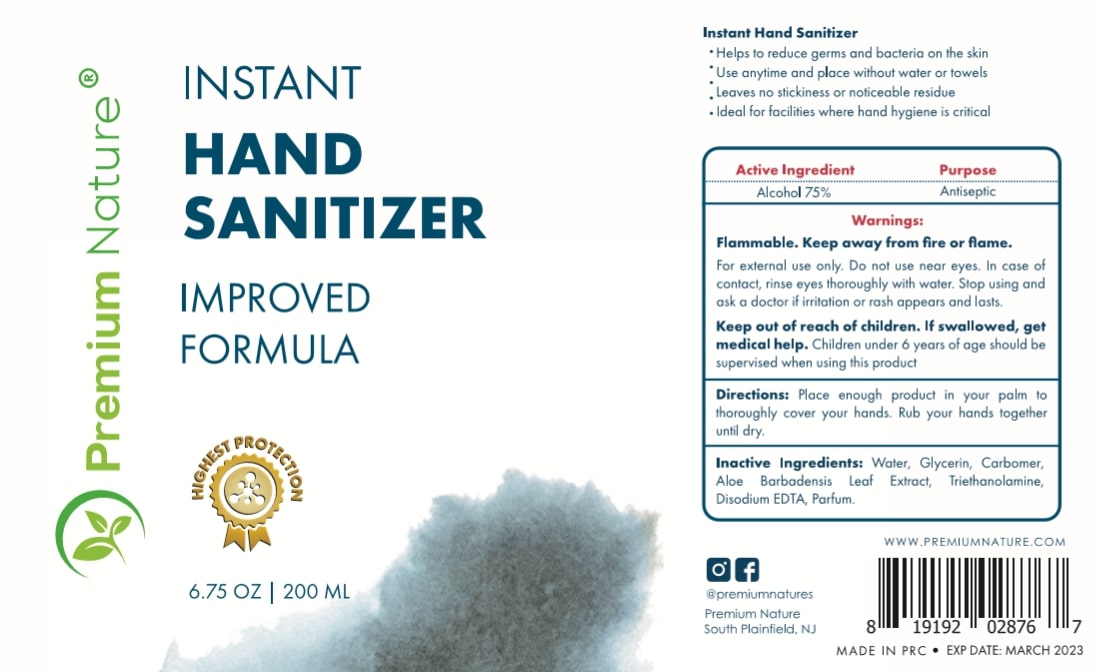 DRUG LABEL: Premium Nature Hand Sanitizer
NDC: 75212-002 | Form: GEL
Manufacturer: Guangzhou Yuncai Fine Chemical CO.LTD
Category: otc | Type: HUMAN OTC DRUG LABEL
Date: 20200509

ACTIVE INGREDIENTS: ALCOHOL 75 mL/100 mL
INACTIVE INGREDIENTS: WATER; GLYCERIN; ALOE VERA LEAF; TROLAMINE; EDETATE DISODIUM ANHYDROUS; CARBOMER HOMOPOLYMER, UNSPECIFIED TYPE

Premium Nature Hand Sanitizer

Active Ingredient

Alcohol 75%

Purpose

Antiseptic

Warnings

Flammable.Keep away from fire or flame.

For external use only.Do not use near eyes.In case of contact, rinse eyes thoroughly with water.Stop using and ask a doctor if irritation or rash appears and lasts.

Keep out of reach of children.

Keep out of reach of children

If swallowed,get medical help.Children under 6 years of age should be supervised when using this product.

Directions

Place enough product in your palm to thoroughly cover your hands.Rub your hands together until dry.

Inactive Ingredients

Water,Glycerin, Carbomer,Aloe Barbadensis Leaf Extract, Triethanolamine,Disodium EDTA, Parfum.